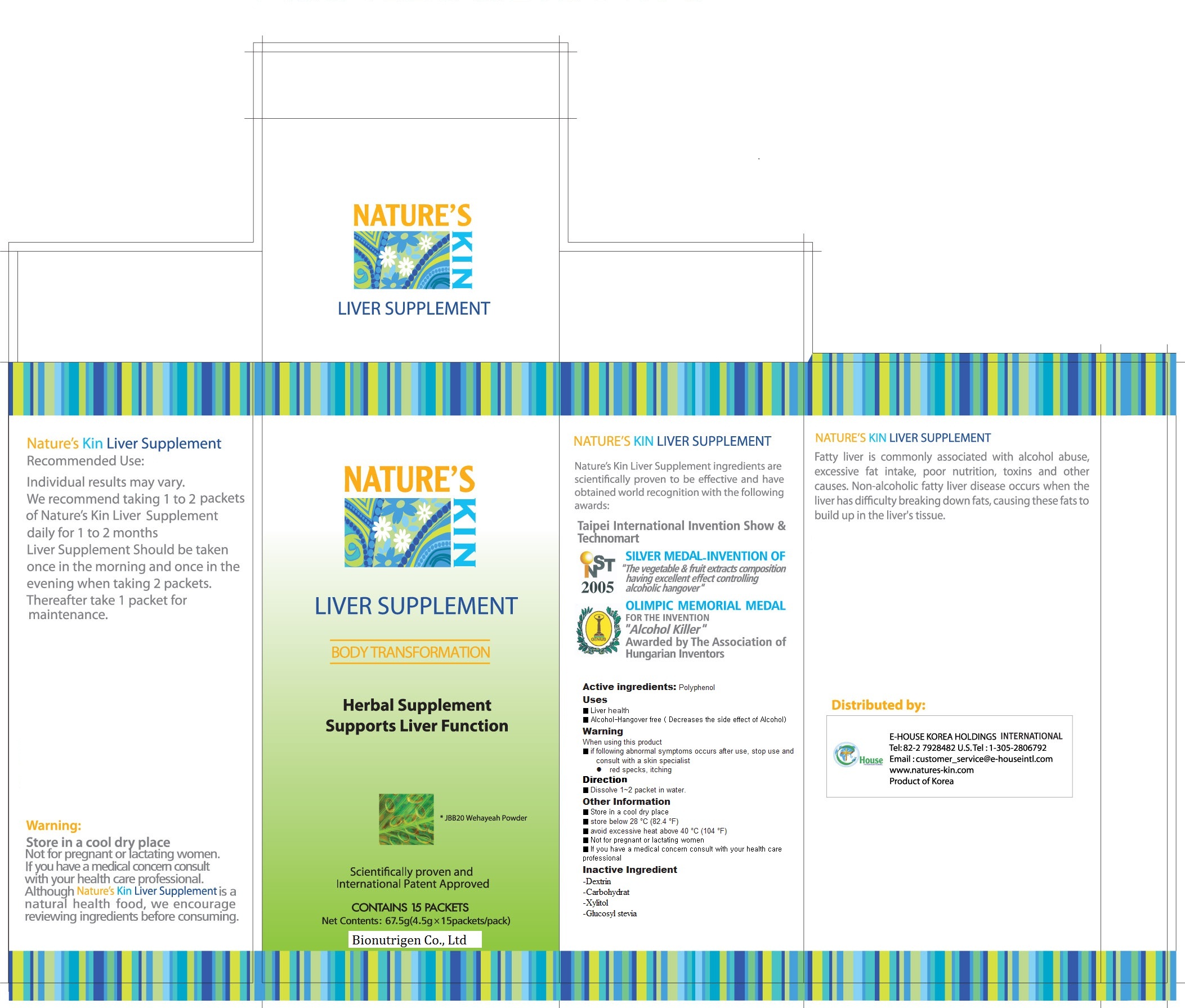 DRUG LABEL: Liver supplement
NDC: 60314-2001 | Form: POWDER
Manufacturer: Bionutrigen Co., Ltd.
Category: otc | Type: HUMAN OTC DRUG LABEL
Date: 20110915

ACTIVE INGREDIENTS: PHENOL 0.8 g/100 g
INACTIVE INGREDIENTS: DEXTROSE; GLUCOSYL STEVIOL; XYLITOL

Drug Facts

active ingredient: polyphenol

inactive ingredient: dextrin, taurine, crude protein, calcium niacin, folic acid vitamin B6, xylitol, glucosyl stevia

PURPOSE

- liver health
- alcohol hangover free
- relieve fatigue

keep out of reach of the children

INDICATIONS AND USAGE

dissolve 1~2 packets in water
take 1~2 packets daily

WARNINGS

- store in a cool dry place
- stop to use if following abnormal systoms occurs, red specks, itching

DOSAGE AND ADMINISTRATION

take this medicine before drinking for best results